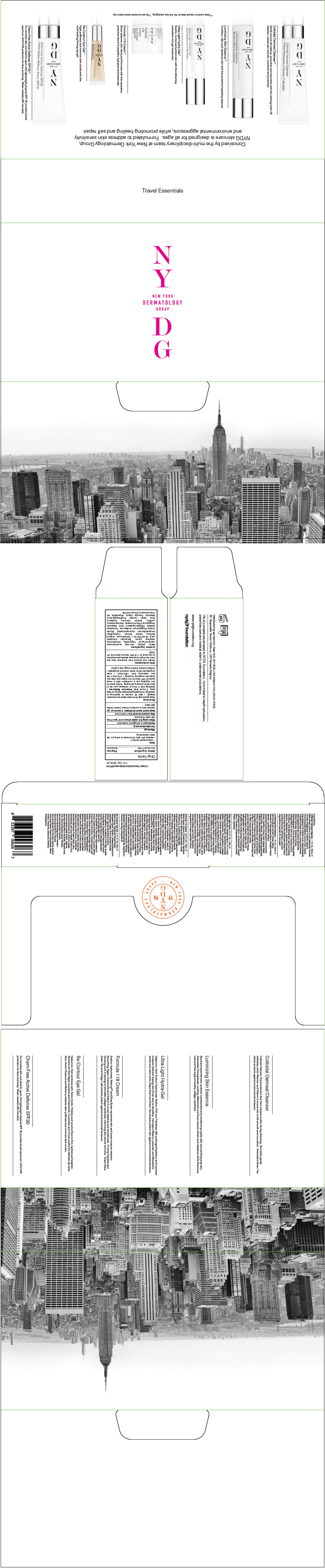 DRUG LABEL: NYDG Travel Essentials
NDC: 71994-009 | Form: KIT | Route: TOPICAL
Manufacturer: Van Laere LLC
Category: otc | Type: HUMAN OTC DRUG LABEL
Date: 20180308

ACTIVE INGREDIENTS: Zinc Oxide 175 mg/1 mL
INACTIVE INGREDIENTS: Water; Isononyl Isononanoate; Butyloctyl Salicylate; MEDIUM-CHAIN TRIGLYCERIDES; Dimethicone; Hexylene Glycol; CETYL PEG/PPG-10/1 DIMETHICONE (HLB 2); ARGAN OIL; HYDROXYETHYL ACRYLATE/SODIUM ACRYLOYLDIMETHYL TAURATE COPOLYMER (100000 MPA.S AT 1.5%); Polyglyceryl-4 Isostearate; .ALPHA.-TOCOPHEROL ACETATE; POLYGLYCERYL-3 RICINOLEATE; POLYHYDROXYSTEARIC ACID (2300 MW); Squalane; Phenoxyethanol; Isostearic Acid; LECITHIN, SOYBEAN; Sodium Chloride; Hexyl Laurate; Ethylhexylglycerin; LEVOMENOL; Caprylyl Glycol; Polysorbate 60; Chlorphenesin; EDETATE DISODIUM; Farnesol

NYDG Travel Essentials

Drug Facts

Active Ingredient

Zinc Oxide 17.5%

Purpose

Sunscreen

Uses

- Helps prevent sunburn
- Retains SPF after 80 minutes of activity in the water or perspiring

Warnings

For external use only

Do not use on damaged or broken skin

When using this product keep out of eyes. Rinse with water to remove

Stop use and ask a doctor if rash occurs

Keep out of reach of children. If swallowed, get medical help or contact a Poison Control Centre right away

Directions

Apply generously 15 minutes before sun exposure.

Reapply:

- after 80 minutes of swimming or sweating
- immediately after towel drying
- at least every 2 hours

Sun Protection Measures

- Spending time in the sun increases your risk of skin cancer and early skin aging. To decrease this risk, regularly use a sunscreen with a broad spectrum SPF value of 15 or higher and other sun protection measures including:
  - limit time in the sun, especially from 10am–2pm
  - wear long-sleeved shirts, pants, hats and sunglasses
- Children under 6 months of age: Ask a doctor

Other information

Protect this product from excessive heat and direct sun. Report a serious adverse event reaction to: van laere llc. 119 Fifth Avenue, New York, NY 10003

Inactive Ingredients

Water (Aqua), Isononyl Isononanoate, Caprylic/Capric Triglyceride, Dimethicone, Hexylene Glycol, Butyloctyl Salicylate, Cetyl PEG/PPG-10/1 Dimethicone, Argania Spinosa Kernel Extract, Hydroxyethyl Acrylate/Sodium Acryloyldimethyl Taurate Copoly Polyglyceryl-4 Isostearate, Tocopheryl Acetate, Polyhydroxystearic Acid, Squalane, Polyglyceryl-3-Poyricinoleate, Phenoxyethanol, Lecithin, Sodium Chloride, Isostearic Acid, Hexyl Laurate Ethylhexylglycerin, Bisabolol, Caprylyl Glycol, Polysorbate 60, Chlorphenesin, Disodium EDTA

Distributed by van laere llc, New York, NY10003, USA

PRINCIPAL DISPLAY PANEL - Kit Carton

N
Y
NEW YORK
DERMATOLOGY
GROUP
D
G